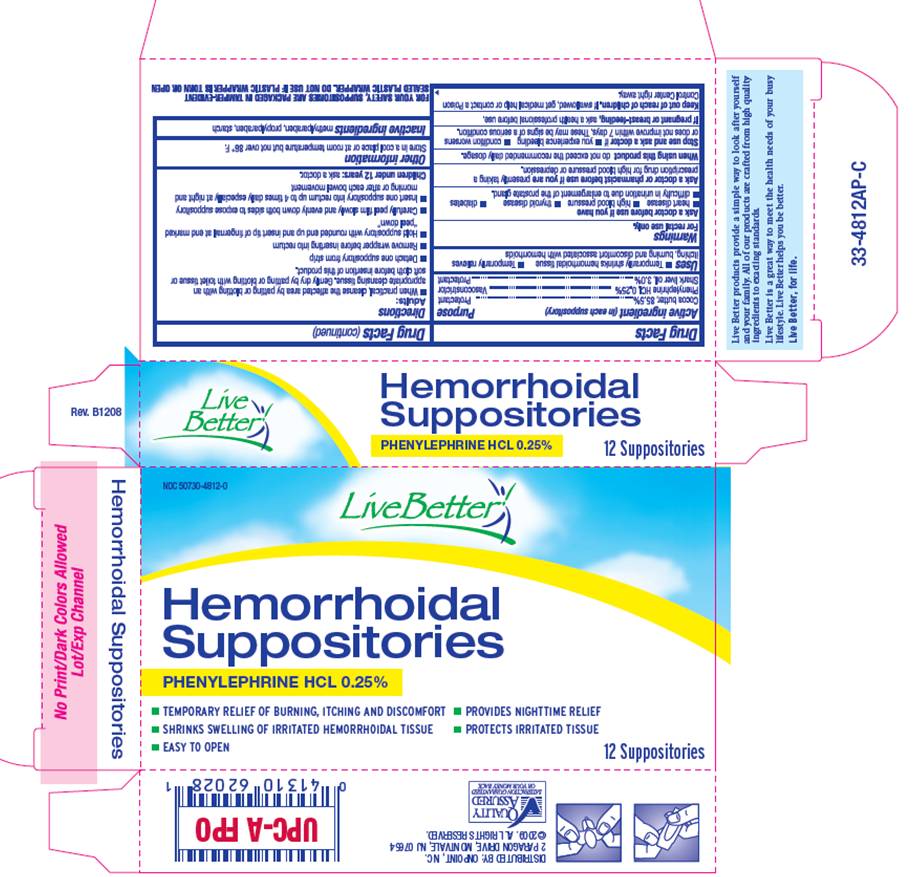 DRUG LABEL: phenylephrine hydrochloride
NDC: 50730-4812 | Form: SUPPOSITORY
Manufacturer: H and P Industries, Inc. dba Triad Group
Category: otc | Type: HUMAN OTC DRUG LABEL
Date: 20091207

ACTIVE INGREDIENTS: cocoa butter 2077 mg/1 1; phenylephrine hydrochloride 6 mg/1 1; shark liver oil 73 mg/1 1
INACTIVE INGREDIENTS: methylparaben; propylparaben; starch, corn

DRUG FACTS

ACTIVE INGREDIENTS

Cocoa butter, 85.5%
Phenylephrine HCI, 0.25%
Shark liver oil, 3.0%

PURPOSE

protectant

vasoconstrictor

protectant

USES

- temporarily shrinks hemorrhoidal tissue
- temporarily relieves itching burning and discomfort associated with hemorrhoids

WARNINGS

For rectal use only.

Ask a doctor before use if you have

- heart disease
- thyroid disease
- difficulty in urination due to enlargement of the prostate gland
- high blood pressure
- diabetes

Ask a doctor or pharmacist before use if

you are presently taking a prescription drug for high blood pressure or depression.

When using this product

do not exceed the recommended daily dosage.

Stop use and ask a doctor if

- you experience bleeding
- condition worsens or does not improve within 7 days.

These may be signs of a serious condition.

If pregnant or breastfeeding

ask a health professional before use.

Keep out of reach of children

If swallowed, get medical help or contact a Poison Control Center right away.

DIRECTIONS

Adults:

- When practical, cleanse the affected area by patting or blotting with an appropriate cleansing tissue. Gently dry by patting or blotting with toilet tissue or soft cloth before insertion of this product.
- Detach one suppository from strip
- Remove wrapper before inserting into rectum
- Hold suppository with rounded end up and insert tip of fingernail at end marked "peel down"
- Carefully peel film slowly and evenly down both sides to expose suppository
- Insert one suppository into rectum up to 4 times daily especially at night and morning or after each bowel movement

Children under 12 years: ask a doctor

STORAGE

Store in a cool place or at room temperature but not over 86° F.

INACTIVE INGREDIENTS

methylparaben, propylparaben, starch

PACKAGE INFORMATION

NDC 50730-4812-0
Live Better
Hemorrhoidal
Suppositories
PHENYLEPHRINE HCL 0.25%

- Temporary relief of burning, itching and discomfort
- Provides nighttime relief
- Shrinks swelling of irritated hemorrhoidal tissue
- Protects irritated tissue
- Easy to open

12 Suppositories
DISTRIBUTED BY OMNIPOINT, INC.
2 PARAGON DRIVE, MONTVALE, NJ 07654
2009 ALL RIGHTS RESERVED
Live Better products provide a simple way to look after yourself
and your family. All of our products are crafted from high quality
ingredients to exacting standards.
Live Better is a great way to meet the health needs of your busy
lifestyle. Live Better helps you be better.
Live Better, for life.
FOR YOUR SAFETY, SUPPOSITORIES ARE PACKAGED IN TAMPER-EVIDENT SEALED PLASTIC WRAPPER.
DO NOT USE IF PLASTIC WRAPPER IS TORN OR OPEN.